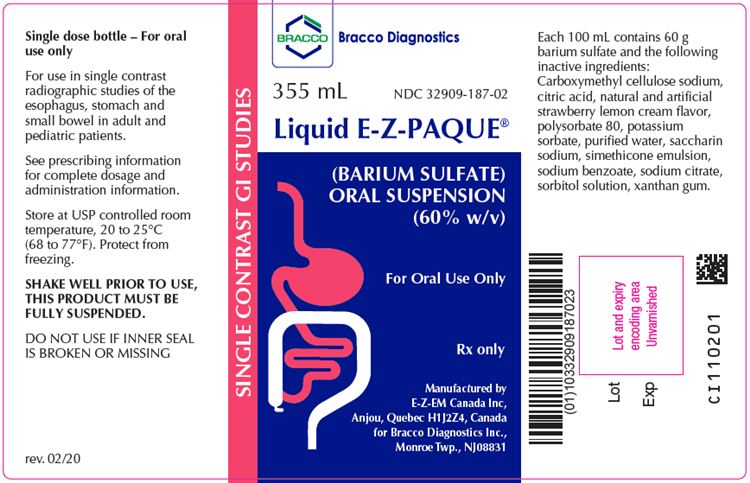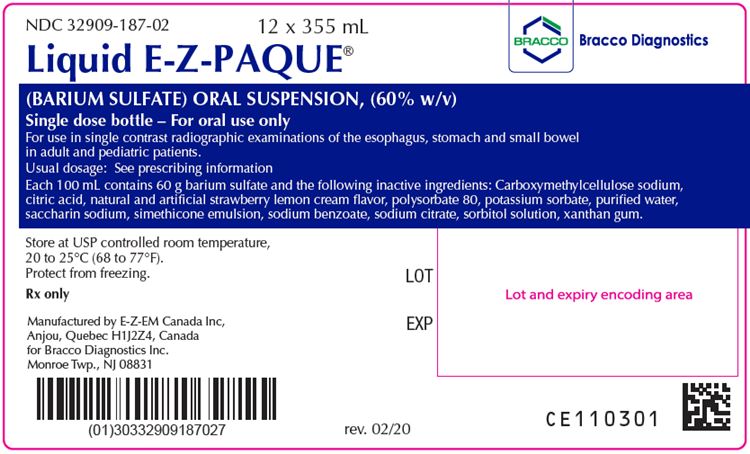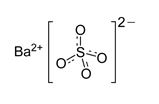 DRUG LABEL: E-Z-Paque
NDC: 32909-186 | Form: SUSPENSION
Manufacturer: E-Z-EM Canada Inc
Category: prescription | Type: HUMAN PRESCRIPTION DRUG LABEL
Date: 20201009

ACTIVE INGREDIENTS: Barium Sulfate 0.6 g/1 mL
INACTIVE INGREDIENTS: CARBOXYMETHYLCELLULOSE SODIUM; ANHYDROUS CITRIC ACID; DIMETHICONE 350; DIMETHICONE 1000; POLYSORBATE 80; POTASSIUM SORBATE; WATER; SACCHARIN SODIUM; SILICON DIOXIDE; SODIUM BENZOATE; TRISODIUM CITRATE DIHYDRATE; SORBITOL; XANTHAN GUM

HIGHLIGHTS OF PRESCRIBING INFORMATION

These highlights do not include all the information needed to use Liquid E-Z-PAQUE safely and effectively. See full prescribing information for Liquid E-Z-PAQUE.
Liquid E-Z-PAQUE (barium sulfate) oral suspension
Initial U.S. Approval: 2016

1 INDICATIONS AND USAGE

Liquid E-Z-PAQUE is a radiographic contrast agent indicated for use in single contrast radiographic examinations of the esophagus, stomach, and small bowel to visualize the gastrointestinal (GI) tract in adult and pediatric patients (1)

2 DOSAGE AND ADMINISTRATION

- Adults: Recommended oral dose is 150 mL to 750 mL (87g to 435g of barium sulfate, respectively) (2.1)
- Pediatric patients: adjust dose based on relative GI volume (2.1)

3 DOSAGE FORMS AND STRENGTHS

- Oral suspension 213 g barium sulfate (60% w/v) (3)

4 CONTRAINDICATIONS

- Known or suspected perforation of the GI tract (4)
- Known obstruction of the GI tract (4)
- Conditions associated with high risk of GI perforation or aspiration (4)
- Known severe hypersensitivity to barium sulfate or any of the excipients of Liquid E-Z-PAQUE (4)

5 WARNINGS AND PRECAUTIONS

- Hypersensitivity reactions: Emergency equipment and trained personnel should be immediately available (5.1)
- Intra-abdominal barium leakage: May occur in conditions such as GI fistula, ulcer, inflammatory bowel disease, appendicitis or diverticulitis, severe stenosis or obstructing lesions of the GI tract (5.2)
- Delayed GI transit and obstruction: Patients should maintain adequate hydration in days following a barium sulfate procedure to avoid obstruction or impaction (5.3)
- Aspiration pneumonitis: Patients with history of food aspiration or with swallowing disorders are at increased risk (5.4)

6 ADVERSE REACTIONS

Common adverse reactions include nausea, vomiting, diarrhea and abdominal cramping (6)

To report SUSPECTED ADVERSE REACTIONS, contact Bracco Diagnostics Inc at 1-800-257-5181 or FDA at 1-800-FDA-1088 or www.fda.gov/medwatch

FULL PRESCRIBING INFORMATION

1 INDICATIONS AND USAGE

Liquid E-Z-PAQUE is indicated for use in single contrast radiographic examinations of the esophagus, stomach, and small bowel to visualize the gastrointestinal (GI) tract in adult and pediatric patients.

2 DOSAGE AND ADMINISTRATION

2.1 Recommended Dosage

The optimal oral dose of Liquid E-Z-PAQUE will vary depending on the size and anatomy of the patient and the procedure being performed. The recommended oral dose of Liquid E-Z-PAQUE:

- Adults: 150 to 750 mL (87 g to 435 g of barium sulfate, respectively). Volumes closer to 150 mL are recommended for examination of the esophagus and stomach and volumes up to 750 mL are recommended for examination of the small bowel
- Pediatric Patients: Adjust dose based on GI volume
  - For examinations of the upper GI tract, administer a volume sufficient to fully distend the esophagus or stomach.
  - For small bowel examinations:
    - Age birth to less than 2 years: 30 mL to 75 mL
    - Age 2 years to less than 17 years: 75 mL to 480 mL

2.2 Administration Instructions

- For oral use only
- Shake bottle vigorously for 30 seconds prior to oral administration to fully suspend product
- Administer undiluted
- Ensure patients have nothing by mouth for the following time period prior to the examination:
  - Neonates and Infants < 3 months                 2 hours
  - Infants 3-12 months                                       3 hours
  - > 12 months of age                                       4 hours
- Discard any unused suspension
- Encourage patients to maintain hydration following the barium sulfate procedure

3 DOSAGE FORMS AND STRENGTHS

Liquid E-Z-PAQUE oral suspension: 213 grams of barium sulfate supplied as a suspension (60 % w/v) in a single-dose bottle.

4 CONTRAINDICATIONS

Liquid E-Z-PAQUE is contraindicated in patients with the following conditions:

- known or suspected perforation of the GI tract
- known obstruction of the GI tract
- high risk of GI perforation such as those with a recent GI perforation, acute GI hemorrhage or ischemia, toxic megacolon, severe ileus, post GI surgery or biopsy, acute GI injury or burn, or recent radiotherapy to the pelvis
- high risk of aspiration such as those with prior aspiration, tracheo-esophageal fistula, or obtundation
- known severe hypersensitivity to barium sulfate or any of the excipients of Liquid E-Z-PAQUE

5 WARNINGS AND PRECAUTIONS

5.1 Hypersensitivity Reactions

Barium sulfate preparations contain a number of excipients, including natural and artificial flavors and may induce serious hypersensitivity reactions. The manifestations include hypotension, bronchospasm and other respiratory impairments, dermal reactions including rashes, urticaria and itching. A history of bronchial asthma, atopy or a previous reaction to a contrast agent may increase the risk for hypersensitivity reactions. Emergency equipment and trained personnel should be immediately available for treatment of a hypersensitivity reaction.

5.2 Intra-abdominal Barium Leakage

The use of Liquid E-Z-PAQUE is contraindicated in patients at high risk of perforation of the GI tract [see Contraindications (4)]. Administration of Liquid E-Z-PAQUE may result in leakage of barium from the GI tract in the presence of conditions such as carcinomas, GI fistula, inflammatory bowel disease, gastric or duodenal ulcer, appendicitis, diverticulitis, and in patients with a severe stenosis at any level of the GI tract, especially distal to the stomach. Barium leakage has been associated with peritonitis and granuloma formation.

5.3 Delayed Gastrointestinal Transit and Obstruction

Orally administered barium sulfate may accumulate proximal to a constricting lesion of the colon, causing obstruction or impaction with development of baroliths (inspissated barium associated with feces) and may cause abdominal pain, appendicitis, bowel obstruction, or rarely perforation. Patients with the following conditions are at higher risk for developing obstruction or baroliths: severe stenosis at any level of the GI tract, impaired GI motility, electrolyte imbalance, dehydration, on a low residue diet, on medications that delay GI motility, constipation, cystic fibrosis or Hirschsprung disease, and the elderly [see Use in Specific Populations (8.4, 8.5)]. To reduce the risk of delayed GI transit and obstruction, patients should maintain adequate hydration following a barium sulfate procedure.

5.4 Aspiration Pneumonitis

The use of Liquid E-Z-PAQUE is contraindicated in patients at high risk of aspiration [see Contraindications (4)]. Oral administration of barium is associated with aspiration pneumonitis, especially in patients with a history of food aspiration or with compromised swallowing mechanism. Vomiting following oral administration of barium sulfate may lead to aspiration pneumonitis. In patients at risk for aspiration, begin the procedure with a small ingested volume of Liquid E-Z-PAQUE. Discontinue administration of Liquid E-Z-PAQUE immediately if aspiration is suspected.

5.5 Systemic Embolization

Barium sulfate products may occasionally intravasate into the venous drainage of the large bowel and enter the circulation as a "barium embolus" leading to potentially fatal complications which include systemic and pulmonary embolism, disseminated intravascular coagulation, septicemia and prolonged severe hypotension. Although this complication is exceedingly uncommon after oral administration of barium sulfate suspension, monitor patients for potential intravasation when administering barium sulfate.

5.6 Risk with Hereditary Fructose Intolerance

Liquid E-Z-PAQUE contains sorbitol which may cause severe symptoms if ingested by patients with hereditary fructose intolerance. Severe symptoms may include the following: vomiting, hypoglycemia, jaundice, hemorrhage, hepatomegaly, hyperuricemia, and kidney failure. Before administration of Liquid E-Z-PAQUE assess patients for a history of hereditary fructose intolerance and avoid use in these patients.

6 ADVERSE REACTIONS

The following adverse reactions have been identified from spontaneous reporting or clinical studies of barium sulfate administered orally. Because the reactions are reported voluntarily from a population of uncertain size, it is not always possible to reliably estimate their frequency or to establish a causal relationship to drug exposure:

- Nausea, vomiting, diarrhea and abdominal cramping
- Serious adverse reactions and fatalities include aspiration pneumonitis, barium sulfate impaction, intestinal perforation with consequent peritonitis and granuloma formation, vasovagal and syncopal episodes

8 USE IN SPECIFIC POPULATIONS

8.1 Pregnancy

Risk Summary
Liquid E-Z-PAQUE is not absorbed systemically following oral administration, and maternal use is not expected to result in fetal exposure to the drug [see Clinical Pharmacology (12.3)].

8.2 Lactation

Risk Summary
Liquid E-Z-PAQUE is not absorbed systemically by the mother following oral administration, and breastfeeding is not expected to result in exposure of the infant to Liquid E-Z-PAQUE [see Clinical Pharmacology (12.3).

8.4 Pediatric Use

The efficacy of Liquid E-Z-PAQUE in pediatric patients from birth to less than 17 years of age is based on successful opacification of the esophagus, stomach, and small bowel during single contrast radiographic procedures [see Clinical Pharmacology (12.1)]. Safety and dosing recommendations in pediatric patients are based on clinical experience [see Dosage and Administration (2.1)].

Liquid E-Z-PAQUE is contraindicated in pediatric patients with tracheo-esophageal fistula. [see Contraindications (4)]. Pediatric patients with a history of asthma or food allergies may be at increased risk for development of hypersensitivity reactions [see Warnings and Precautions (5.1)]. Monitor pediatric patients with cystic fibrosis or Hirschsprung disease for bowel obstruction after use [see Warnings and Precautions (5.3)]

8.5 Geriatric Use

Clinical studies of Liquid E-Z-PAQUE do not include sufficient numbers of subjects aged 65 and over to determine whether they respond differently from younger subjects. Other reported clinical experience has not identified differences in responses between the elderly and younger patients. In general, dose selection for an elderly patient should be cautious, usually starting at the low end of the dosing range, reflecting the greater frequency of decreased hepatic, renal, or cardiac function, and of concomitant disease or other drug therapy.

11 DESCRIPTION

Liquid E-Z-PAQUE (barium sulfate) is a radiographic contrast agent supplied as a white to lightly colored barium sulfate suspension (60%w/v) for oral administration. The active ingredient barium sulfate is designated chemically as BaSO4 with a molecular weight of 233.4 g/mol, a density of 4.5 g/cm^3, and the following chemical structure:

Liquid E-Z-PAQUE contains the following excipients: carboxymethyl cellulose sodium, citric acid, natural and artificial strawberry lemon cream flavor, polysorbate 80, potassium sorbate, purified water, saccharin sodium, simethicone emulsion, sodium benzoate, sodium citrate, sorbitol solution, xanthan gum.

12 CLINICAL PHARMACOLOGY

12.1 Mechanism of Action

Due to its high atomic number, barium (the active ingredient in Liquid E-Z-PAQUE) is opaque to x-rays and therefore acts as a positive contrast agent for radiographic studies.

12.3 Pharmacokinetics

Under physiological conditions, barium sulfate passes through the gastrointestinal tract in an unchanged form and is absorbed only in pharmacologically insignificant amounts.

13 NONCLINICAL TOXICOLOGY

13.1 Carcinogenesis, Mutagenesis, Impairment of Fertility

No animal studies have been performed to evaluate the carcinogenic potential of barium sulfate or potential effects on fertility.

16 HOW SUPPLIED/STORAGE AND HANDLING

How Supplied
Liquid E-Z-PAQUE (barium sulfate) is a suspension (60% w/v) supplied as a unit dose in a single use HDPE plastic bottle containing 213 grams of barium sulfate in 355 mL.

Provided as: 12 x 355 mL bottles (NDC 32909-187-02).

Storage and Handling
Store at USP controlled room temperature 20 to 25°C (68 to 77° F). Protect from freezing.

17 PATIENT COUNSELING INFORMATION

After administration advise patients to:

- Maintain adequate hydration
- Seek medical attention for worsening of constipation or slow gastrointestinal passage
- Seek medical attention for any delayed onset of hypersensitivity, such as: rash, urticaria, or respiratory difficulty

Manufactured for
Bracco Diagnostics Inc.
Monroe Township, NJ 08831
by EZEM Canada Inc
Anjou (Quebec) Canada H1J 2Z4

Revised February 2020

CL110101

PACKAGE LABEL

LIQUID E-Z-PAQUE 355 mL Carton and Label
NDC: 32909-187-02